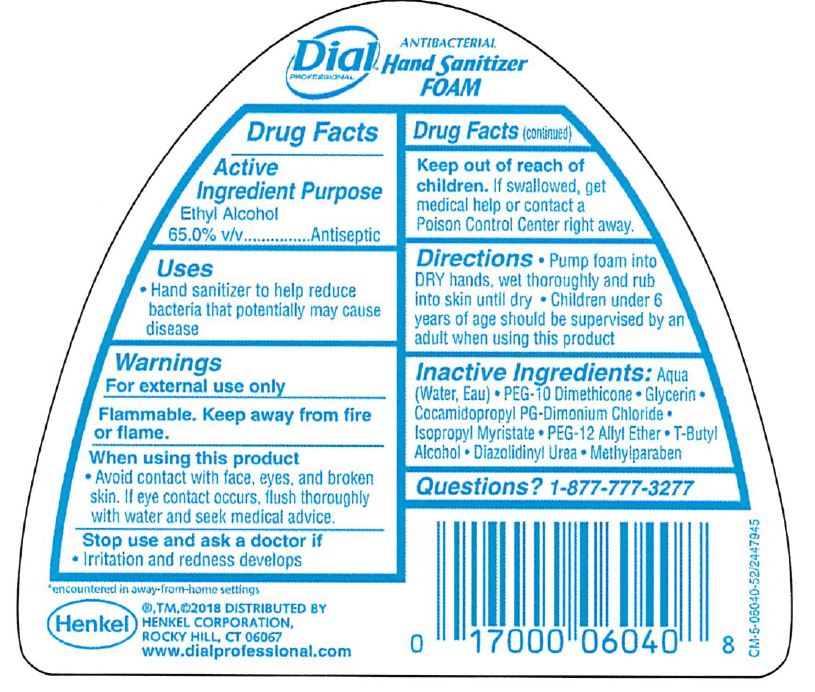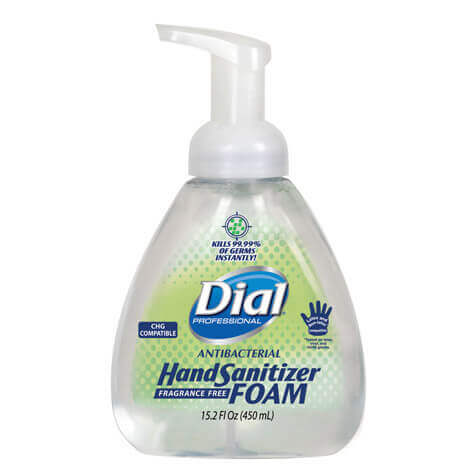 DRUG LABEL: dial Professional Foaming Hand Sanitizer
NDC: 50663-004 | Form: LIQUID
Manufacturer: Zotos International Inc
Category: otc | Type: HUMAN OTC DRUG LABEL
Date: 20200501

ACTIVE INGREDIENTS: ALCOHOL 62.75 mL/100 mL
INACTIVE INGREDIENTS: ISOPROPYL MYRISTATE; METHYLPARABEN; PEG-10 DIMETHICONE (600 CST); COCAMIDOPROPYL PG-DIMONIUM CHLORIDE; TERT-BUTYL ALCOHOL; DIAZOLIDINYL UREA; GLYCERIN 0.857 mL/100 mL; WATER 33.97 mL/100 mL

Dial Professional Foaming Hand Sanitizer

Active Ingredient(s)

Ethyl Alcohol 65% v/v. Purpose: Antiseptic

Purpose

Antiseptic, Hand Sanitizer

Use

Hand Sanitizer to help reduce bacteria that potentially can cause disease.

Warnings

For external use only. Flammable. Keep away from fire or flame

When using this product avoid contact with face, eyes, and broken skin. if eye contact occurs, flush thoroughly with water and seek medical advice.

Stop use and ask a doctor if irritation or redness develops.

Keep out of reach of children. If swallowed, get medical help or contact a Poison Control Center right away.

Directions

- Put foam into DRY hands, wet hands thoroughly and rub into skin until dry.
- Children under 6 years of age should be supervised by an adult when using this product.

Inactive ingredients

Aqua (Water, Eau)· PEG-10 Dimethicone · Glycerin · Cocamidopropyl PG-Dimonium Chloride· lsopropyl Myristate ·
PEG-12 Allyl Ether· T-Butyl Alcohol · Diazolidinyl Urea · Methylparaben

Questions

1-877-777-3277

Legal Entity

®,TM,©2018 Distributed by
Henkel Corporation,
Rocky Hill, CT 06067
www.dialprofessional.com

Package Label - Principal Display Panel

450 mL NDC: 50663-004-01